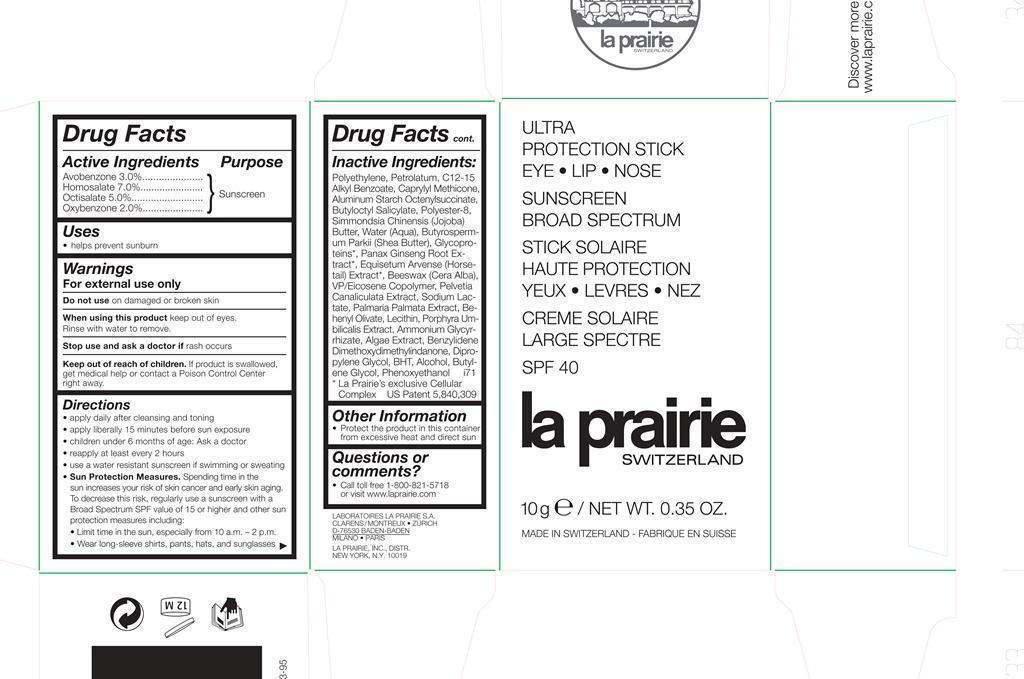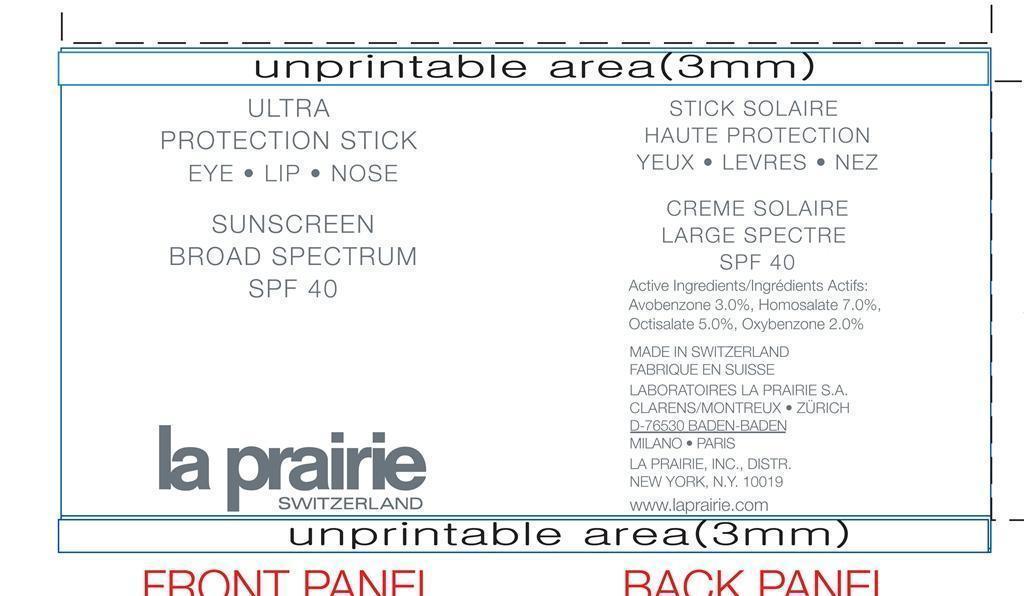 DRUG LABEL: Ultra Protection Stick Broad Spectrum SPF 40
NDC: 68807-323 | Form: STICK
Manufacturer: Temmentec Ag
Category: otc | Type: HUMAN OTC DRUG LABEL
Date: 20160125

ACTIVE INGREDIENTS: AVOBENZONE 3 g/100 kg; HOMOSALATE 7 g/100 kg; OCTISALATE 5 g/100 kg; OXYBENZONE 2 g/100 kg
INACTIVE INGREDIENTS: POLYETHYLENE GLYCOL 350; PETROLATUM; ALKYL (C12-15) BENZOATE; ALUMINUM STARCH OCTENYLSUCCINATE; BUTYLOCTYL SALICYLATE; POLYESTER-8 (1400 MW, CYANODIPHENYLPROPENOYL CAPPED); JOJOBA BUTTER; WATER; SHEA BUTTER; ASIAN GINSENG; WHITE WAX; PELVETIA CANALICULATA; SODIUM LACTATE; DULSE; BEHENYL OLIVATE; LECITHIN, SOYBEAN; PORPHYRA UMBILICALIS; AMMONIUM GLYCYRRHIZATE; BENZYLIDENE DIMETHOXYDIMETHYLINDANONE; DIPROPYLENE GLYCOL; BUTYLATED HYDROXYTOLUENE; ALCOHOL; BUTYLENE GLYCOL; PHENOXYETHANOL

Ultra Protection Stick Sunscreen Broad Spctrum SPF 40

Active Ingredients Purpose

Avobenzone 3% Sunscreen

Homosalate 7% Sunscreen

Octisalate 5% Sunscreen

Oxybenzone 2% Sunscreen

Uses

helps prevent sunburn

warning

Keep out of reach of children

Indications

Stop use and ask a doctor if rash occurs

warnings

For external use only

Do not use on damaged or broken skin

When using this product keep out of eyes.

Rinse with water to remove.

Directions

apply daily after cleansing and toning

apply liberally 15 minutes befor e sun exposure

children under 6 months of age: Ask a doctor

reapply at least every 2 hours

use a water resistant sunscreen if swimming or sweating

Sun Protection Measures.

Spending time in the sun increases your risk of skin cancer and early skin aging.

To decrease this risk, regularly use a sunscreen with a Broad Spectrum SPF value of 15 or higher and other sun

protection measures including:

Limit time in the sun, especially from 10 a.m. – 2 p.m.

Wear long-sleeve shirts, pants, hats, and sunglasses

Inactive Ingredients

Polyethylene, Petrolatum, C12-15 Alkyl Benzoate, Caprylyl Methicone, Aluminum Starch Octenylsuccinate, Butyloctyl Salicylate, Polyester-8, Simmondsia Chinensis (Jojoba) Butter, Water (Aqua), ButyrospermumParkii (Shea Butter), Glycoproteins, Panax Ginseng Root Extract, Equisetum Arvense (Horsetail) Extract, Beeswax (Cera Alba), VP/Eicosene Copolymer, Pelvetia Canaliculata Extract, Sodium Lactate, Palmaria Palmata Extract, Behenyl Olivate, Lecithin, Porphyra Umbilicalis Extract, Ammonium Glycyrrhizate, Algae Extract, Benzylidene Dimethoxydimethylindanone, Dipropylene Glycol, BHT, Alcohol, Butylene Glycol, Phenoxyethanol

PACKAGE LABEL

Ultra Protection Stick

Eye - Lip - Nose

Sunscreen Broad Spectrum

Stick Solaire Haute Protection

Yeux - Levres - Nez

Creme Solaire

Large Spectre

SPF 40

la prarie Switzerland

10 g/ Net Wt. 0.35 OZ

Made in Switzerland Fabrique en Suisse